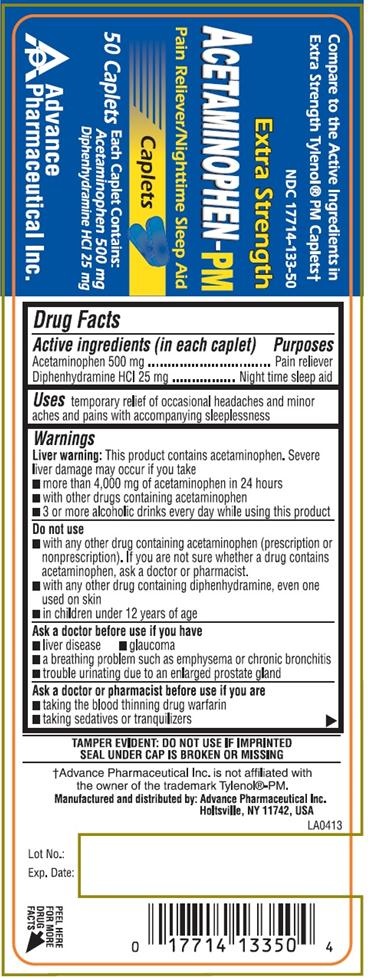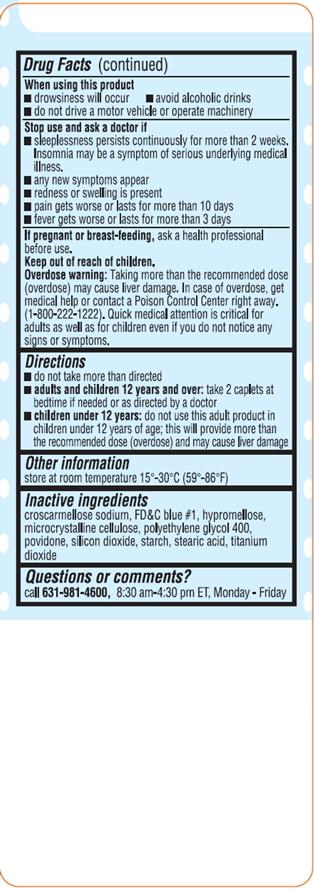 DRUG LABEL: ACETAMINOPHEN PM
NDC: 17714-133 | Form: TABLET
Manufacturer: Advance Pharmaceutical Inc.
Category: otc | Type: HUMAN OTC DRUG LABEL
Date: 20171222

ACTIVE INGREDIENTS: ACETAMINOPHEN 500 mg/1 1; DIPHENHYDRAMINE HYDROCHLORIDE 25 mg/1 1
INACTIVE INGREDIENTS: CROSCARMELLOSE SODIUM; FD&C BLUE NO. 1; HYPROMELLOSES; CELLULOSE, MICROCRYSTALLINE; POLYETHYLENE GLYCOL 400; POVIDONE; SILICON DIOXIDE; STARCH, CORN; STEARIC ACID; TITANIUM DIOXIDE

ACETAMINOPHEN-PM

Active Ingredient

(in each caplet)

Acetaminophen 500 mg

Diphenhydramine HCl 25 mg

Purpose

Pain Reliever / Night time sleep aid

Uses

temporarily relief of occasional headaches and minor aches and pains with accompanying sleeplessness

Warnings

Liver warning: This product contains acetaminophen. Severe liver damage may occur if you take

- more than 4,000 mg of acetaminophen in 24 hours
- with other drugs containing acetaminophen
- 3 or more alcoholic drinks every day while using this product

do not use

- with any other drug containing acetaminophen (prescription or non prescription). If you are not sure whether a drug contains acetaminophen, ask a doctor or pharmacist.
- with any other drug containing diphenhydramine, even one used on skin
- in children under 12 years of age

Ask a doctor before use if the you have

- liver disease
- glaucoma
- a breathing problem such as emphysema or chronic bronchitis
- trouble urinating due to an enlarged prostate gland

Ask a doctor or pharmacist before use if you are

- taking the blood thinning drug warfarin
- taking sedative or tranquilizers

when using this product

- drowsiness will occur
- avoid alcoholic drinks
- do not drive a motor vehicle or operate machinery

Stop use and ask a doctor if

- sleeplessness persists continuously for more than 2 weeks, insomnia may be a symptom of serious underlying medical illness.
- Any new symptoms appear
- redness or swelling is present
- pain gets worse or lasts more than 10 days
- fever gets worse or lasts more than 3 days

If pregnant or breast-feeding, ask a health professional before use.

Keep out of reach of children.

Overdose warning: Taking more than the recommended dose (overdose) may cause liver damage. In case of overdose, get medical help or contact a Poison Control Center right away. (1-800-222-1222) Quick medical attention is critical for adults as well as for children even if you do not notice any signs or symptoms.

Directions

- do not take more than directed
- adults and children 12 years and over: take 2 caplets at bedtime if needed or as directed by a doctor
- children under 12 years : do not use this adult product in children under 12 years of age; this will provide more than the recommended dose(overdose) and may cause liver damage

Other Information

- store at 15-30 °C (59-86 °F)

Inactive Ingredients

crosscarmellose sodium, FD&C blue # 1, hypromellose, microcrystalline cellulose, polyethylene glycol 400, povidone, silicon dioxide, starch, stearic acid, titanium dioxide

Questions or Comments

Call 631-981-4600 8.30 am- 4.30 pm ET, Monday-Friday

TAMPER EVIDENT: DO NOT USE IF IMPRINTED SAFETY SEAL UNDER CAP IS BROKEN OR MISSING

Manufactured by: Advance Pharmaceutical, Inc. Holtsville, NY 11742

PACKAGE LABEL.PRINCIPAL DISPLAY PANEL

NDC: 17714-133-50 – 50 COUNT CAPLETS